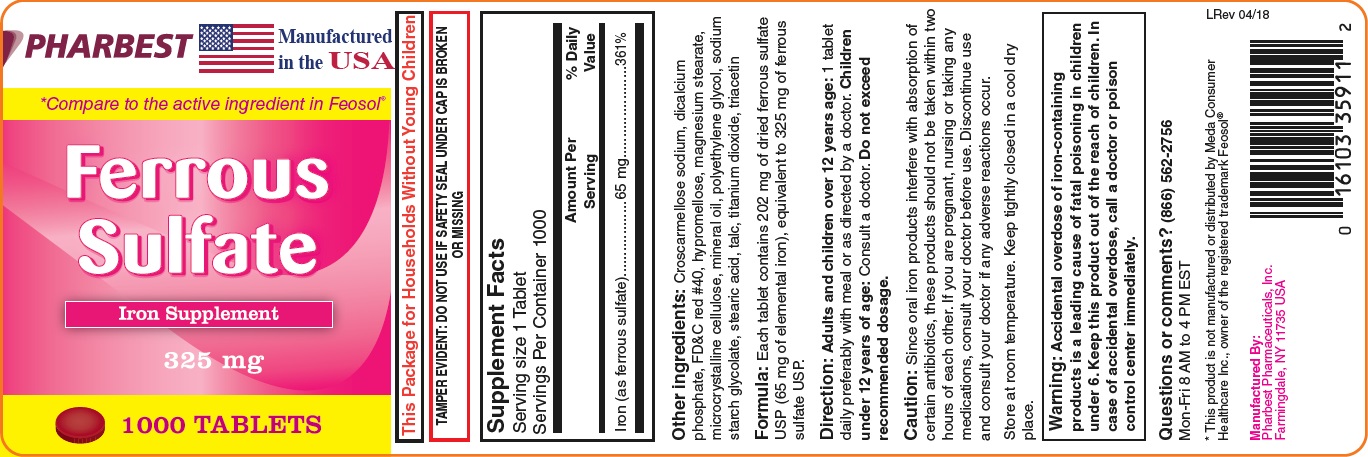 DRUG LABEL: Ferrous Sulfate
NDC: 16103-359 | Form: TABLET, FILM COATED
Manufacturer: Pharbest Pharmaceuticals, Inc.
Category: other | Type: DIETARY SUPPLEMENT
Date: 20210327

ACTIVE INGREDIENTS: FERROUS SULFATE 65 mg/1 1
INACTIVE INGREDIENTS: CROSCARMELLOSE SODIUM; CALCIUM PHOSPHATE, DIBASIC, ANHYDROUS; FD&C RED NO. 40; HYPROMELLOSE, UNSPECIFIED; MAGNESIUM STEARATE; CELLULOSE, MICROCRYSTALLINE; MINERAL OIL; POLYETHYLENE GLYCOL, UNSPECIFIED; SODIUM STARCH GLYCOLATE TYPE A CORN; STEARIC ACID; TALC; TITANIUM DIOXIDE; TRIACETIN

Supplement Facts

Serving Size 1 Tablet

Servings Per Container 1000

 | Amount Per Serving | % Daily Value
Iron (as ferrous sulfate) | 65 mg | 361%

Other ingredients: croscarmellose sodium, dicalcium phosphate, FD&C red #40, hypromellose, magnesium stearate, microcrystalline cellulose, mineral oil, polyethylene glycol, sodium starch glycolate, stearic acid, talc, titanium dioxide, triacetin

Formula: Each tablet contains 202 mg of dried ferrous sulfate USP, equivalent to 325 mg of ferrous sulfate USP (65 mg of elemental iron), equivalent to 325 mg of ferrous sulfate USP.

Directions:

Adults and children over 12 years age: 1 tablet daily preferably with a meal or as directed by a doctor. Children under 12 years of age: consult a doctor. Do not exceed recommended dosage.

Caution:

Since oral iron products interfere with absorption of certain antibiotics, these products should not be taken within two hours of each other. If you are pregnant, nursing or taking any medications, consult your doctor before use. Discontinue use and consult your doctor if any adverse reactions occur.

WARNING: Accidental overdose of iron-containing products is a leading cause of fatal poisoning in children under 6. Keep this product out of the reach of children. In case of overdose, call a doctor or Poison Control Center right immediately.

SAFE HANDLING WARNING

Store at room temperature. Keep tightly closed in a cool dry place.

Questions or comments? (866) 562-2756

PACKAGE LABEL

PHARBEST

Manufactured in the USA

*Compare to the active ingredient in Feosol®

Ferrous

Sulfate

Iron Supplement

325 mg

1000 TABLETS